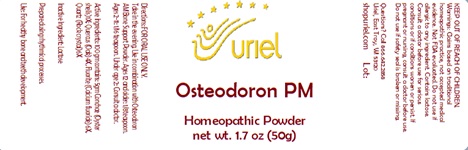 DRUG LABEL: Osteodoron PM
NDC: 48951-7191 | Form: POWDER
Manufacturer: Uriel Pharmacy Inc.
Category: homeopathic | Type: HUMAN OTC DRUG LABEL
Date: 20241216

ACTIVE INGREDIENTS: OSTREA EDULIS SHELL 1 [hp_X]/1 g; SILICON DIOXIDE 6 [hp_X]/1 g; QUERCUS ROBUR WHOLE 4 [hp_X]/1 g; CALCIUM FLUORIDE 6 [hp_X]/1 g
INACTIVE INGREDIENTS: LACTOSE, UNSPECIFIED FORM

Osteodoron PM

INDICATIONS AND USAGE

Directions: FOR ORAL USE ONLY.

DOSAGE AND ADMINISTRATION

Take in the evening. Use in combination with Osteodoron AM Bone Support Powder. Ages 12 and older: 1/8 teaspoon. Ages 2-11: 1/16 teaspoon. Under age 2: Consult a doctor.

ACTIVE INGREDIENT

Active Ingredients: 100 gm contains: 5gm Conchae (Oyster shells) 1X; Quercus (Oak) 4X, Fluorite (Calcium fluoride) 6X, Quartz (Rock crystal) 6X

Inactive Ingredient: Lactose

Prepared using rhythmical processes.

PURPOSE

Use: For healthy bone and teeth development.

KEEP OUT OF REACH OF CHILDREN.

WARNINGS

Warnings: Claims based on traditional homeopathic practice, not accepted medical evidence. Not FDA evaluated. Do not use if allergic to any ingredient. Contains lactose. Consult a doctor before use for serious conditions or if conditions worsen or persist. If pregnant or nursing, consult a doctor before use. Do not use if safety seal is broken or missing.

Questions? Call 866.642.2858
Uriel, East Troy, WI 53120
shopuriel.com Lot: